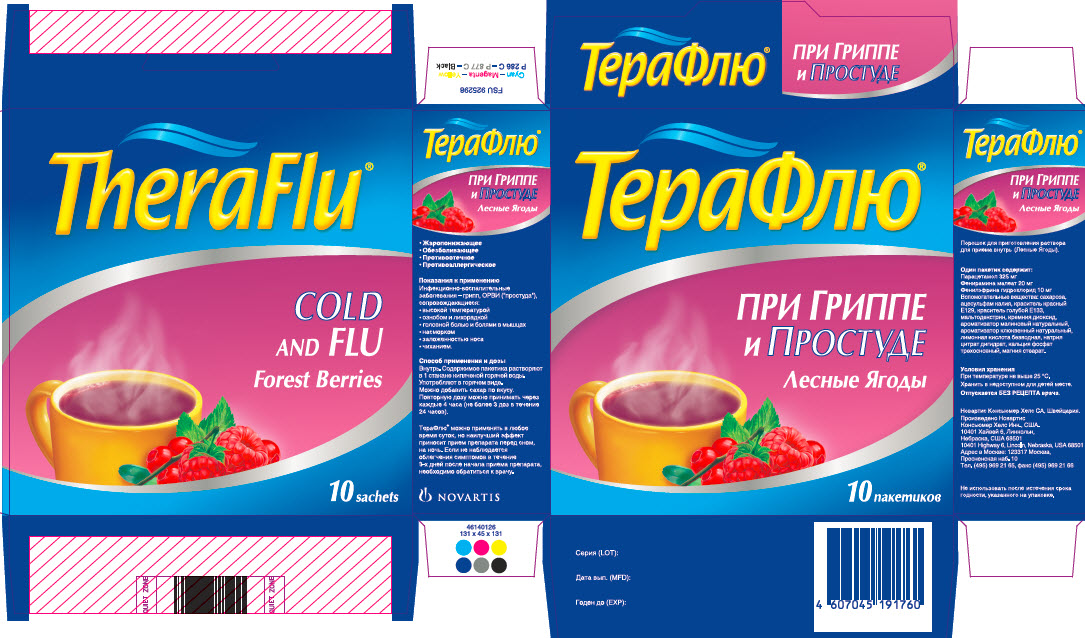 DRUG LABEL: TheraFlu Cold and Flu
NDC: 0067-8135 | Form: POWDER
Manufacturer: Haleon US Holdings LLC
Category: otc | Type: HUMAN OTC DRUG LABEL
Date: 20240424

ACTIVE INGREDIENTS: ACETAMINOPHEN 325 mg/1 1; PHENIRAMINE MALEATE 20 mg/1 1; PHENYLEPHRINE HYDROCHLORIDE 10 mg/1 1
INACTIVE INGREDIENTS: ACESULFAME POTASSIUM; ANHYDROUS CITRIC ACID; FD&C RED NO. 40; FD&C BLUE NO. 1; MAGNESIUM STEARATE; MALTODEXTRIN; SILICON DIOXIDE; SUCROSE; SODIUM CITRATE, UNSPECIFIED FORM; TRIBASIC CALCIUM PHOSPHATE

Drug Facts

TheraFlu® Cold and Flu Forest Berries

Pharmaceutical form:Powder for preparing a solution for internal use (forest berries).

Composition:

One packet contains:

Active ingredients: paracetamol 325 mg, pheniramine maleate 20 mg, phenylephrine hydrochloride 10 mg.

Auxiliary ingredients:

sucrose, acesulfame potassium, red dye Е129, blue dye Е133, maltodextrin, silicon dioxide, flavoring agent natural raspberry, flavoring agent natural cranberry, anhydrous citric acid, sodium citrate dihydrate, tribasic calcium phosphate, magnesium stearate.

Description:

Loose white powder containing white, yellow, and gray-violet granules. May contain soft clumps.

When one packet is dissolved in hot water, a cloudy solution forms which is pink-violet in color with a berry aroma.

Pharmacotherapeutic group:

analgesics and antipyretics, paracetamol in combination with other preparations (excluding psycholeptics).

ATC code:NO2BE51

Pharmacological properties:Combination preparation, has an antipyretic, anti-inflammatory, anti-edematous, analgesic, and anti-allergic action.

Indications:

Infectious/inflammatory illnesses - influenza, ARVI (“common cold”), accompanied by a high temperature, chills, and fever, headache, rhinitis and nasal congestion, sneezing, and muscle pain

Contraindications:

Increased sensitivity to individual ingredients of the preparation, simultaneous use of tricyclic antidepressants, monoamine oxidase (MAO) inhibitors, beta-adrenergic blockers; portal hypertension; alcoholism; diabetes mellitus, pregnancy, breast-feeding, children under 12 years of age.

With caution: in marked coronary artery atherosclerosis, in arterial hypertension, narrow-angle glaucoma, severe liver or kidney diseases, prostatic hyperplasia, blood diseases, glucose-6-phosphate dehydrogenase deficiency, congenital hyperbilirubinemia (Gilbert, Dubin-Johnson, and Rotor syndromes), hyperthyroidism, pheochromocytoma, bronchial asthma.

Dosage and administration:

Oral. The content of a packet is dissolved in 1 glass of boiling hot water. Consumed in hot form. Sugar can be added to taste. A repeated dose may be taken every 4 hours (no more than 3 doses in 24 hours).

TheraFlu® can be used at any time of day, but taking the preparation before going to sleep, for the night, has the best effect. If there is no relief of symptoms within 3 days after the preparation is first taken, a physician must be consulted

Side effects:

possible allergic reactions (skin rash, pruritus, hives, angioedema), hyperexcitability, sleep disorder, reduction in the speed of psychomotor reactions, drowsiness, dizziness, nausea, vomiting, stomach pain, palpitations, blood pressure increase, dry mouth, accommodative palsy, increase in intraocular pressure, urinary retention. During prolonged use in high doses - hepatotoxic action, changes in blood count; nephrotoxicity.

Overdosage:

Nausea, vomiting, epigastric pain, hepatotoxic and nephrotoxic action, in severe cases - hepatic insufficiency, hepatic necrosis, increase in "liver" transaminase activity, increase in prothrombin time, encephalopathy, and comatose state.

Treatment: gastric lavage, administration of activated charcoal, symptomatic therapy. Administration of methionine 8-9 hours after the overdosage and N-acetylcysteine - after 12 hours. Medical attention should be sought.

Interaction with other drugs:

Intensifies the effect of MAO inhibitors, sedative preparations, ethanol. The risk of the hepatotoxic action of paracetamol increases during concurrent use of barbiturates, diphenine, carbamazepine, rifampicin, zidovudine, and other hepatic microsomal enzyme inducers. Antidepressants, antiparkinsonian agents, antipsychotic agents, and phenothiazine derivatives - increase the risk of developing urinary retention, dry mouth, and constipation. Glucocorticosteroids increase the risk of developing elevated intraocular pressure.

Special warnings:

To avoid toxic liver damage, the preparation should not be combined with the use of alcoholic beverages. Care should be taken when the preparation is used by individuals over 70 years of age with cardiovascular disease because of the possible vasoconstricting action of phenylephrine.

If regardless of the use of the preparation, the illness is accompanied by continuing fever or repeated temperature elevations, a physician must be consulted.

Do not exceed the recommended dose.

Do not use the preparation from damaged packets.

Effect on the ability to drive an automobile and to operate machinery.

During treatment, care must be taken when operating an automobile or other machinery, requiring mental alertness and quick psychomotor reactions.

Storage conditions:

At a temperature below 25°C.

Shelf life:

2 years. Do not use after the expiration date printed on the package.